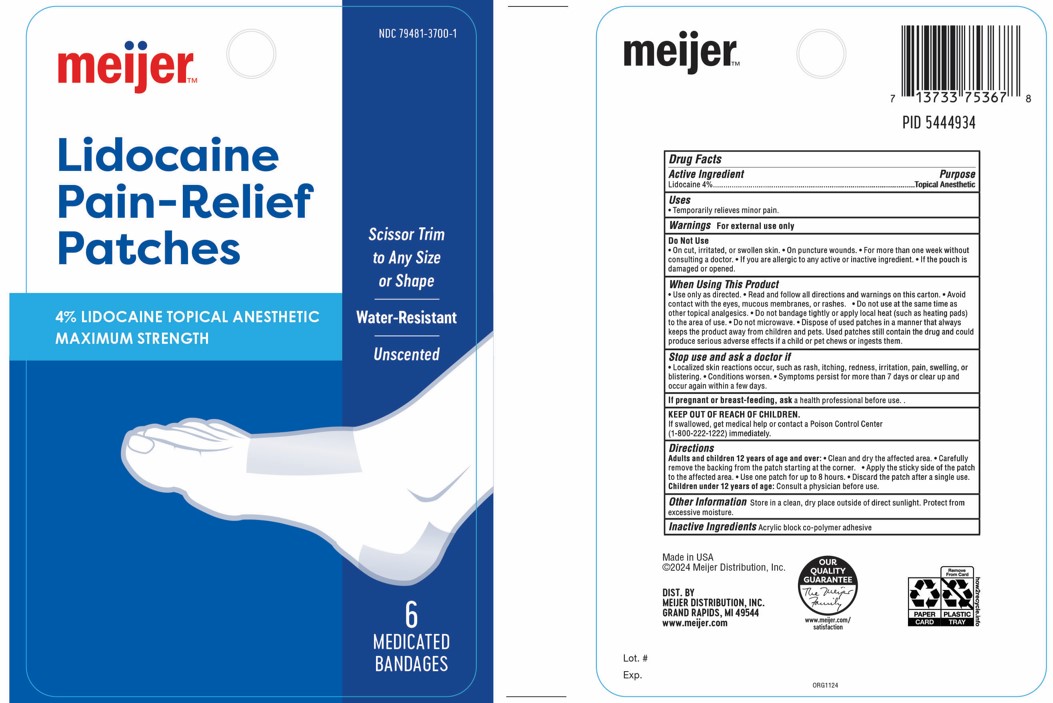 DRUG LABEL: Lidocaine Pain-Relief Patches
NDC: 79481-3700 | Form: PATCH
Manufacturer: Meijer, Inc
Category: otc | Type: HUMAN OTC DRUG LABEL
Date: 20250227

ACTIVE INGREDIENTS: LIDOCAINE 4 mg/100 mg
INACTIVE INGREDIENTS: POLYQUATERNIUM-7 49.6 mg/100 mg

DRUG FACTS

ACTIVE INGREDIENT

Lidocaine 4%

PURPOSE

Topical Anesthetic

INDICATIONS AND USAGE

Temporarily relieves minor pain

WARNINGS

For exteral use only

DO NOT USE

- on cut, irritated, or swollen skin. - On puncture wounds. - For more than one week without consulting a doctor. -If you are allergic to any active or inactive ingredient. - If the pouch is damaged or opened.

WHEN USING

- Use only as directed

- Read and follow all directions and warning on this carton

- Avoid contact with the eyes, mucous membranes, or rashes.

- Do not use at the same time as other topical analgesics.

- Do not bandage tightly or apply local heat (such as heating pads) to the area of use.

- Do not microwave.

- Dispose of used patches in a manner that always keeps the product away from children and pets.

- Used patches still contain the drug and could produce serious adverse effects if a child or pet chews or ingests them.

STOP USE

- Localized skin reaction occur, such as rash, itching, redness, irritation, pain, swelling, or blistering.

- conditions worsen.

- Symptoms persist for more than 7 days or clear up and occur again within a few days.

PREGNANCY OR BREAST FEEDING

Ask a health professional before use.

KEEP OUT OF REACH OF CHILDREN

If swallowed, get medical help or contact a poison Control Center

(1-800-222-1222) immediately.

DOSAGE AND ADMINISTRATION

Adults and children 12 years of age and over:

- Clean and dry the affected area.

- Carefully remove the backing from the patch starting at the corner

- Apply the sticky side of the patch to the affected area.

- Use one patch for up to 8 hours.

- Discard the patch after a single use.

- Chindren under 12 years of age: Consult a physician before use

OTHER SAFETY INFORMATION

Store in a clean, dry place outside of direct sunlight. Protect from excessive moisture.

INACTIVE INGREDIENT

Acrylic block co-polymer adhesve

Dist. By

Meijer Distribution, Inc.

Grand Rapids, MI 49544

www.meijer.com

PACKAGE LABEL

meijer

NDC 79481-3700-1

Lidocain

Pain-Relief

Patches

4% LIDOCAINE TOPICAL ANESTHETIC MAXIMUM STRENGTH

Scissor Trim to Any Size or Shape

Water-Resistant

Uncented

6

Medicated Bandages